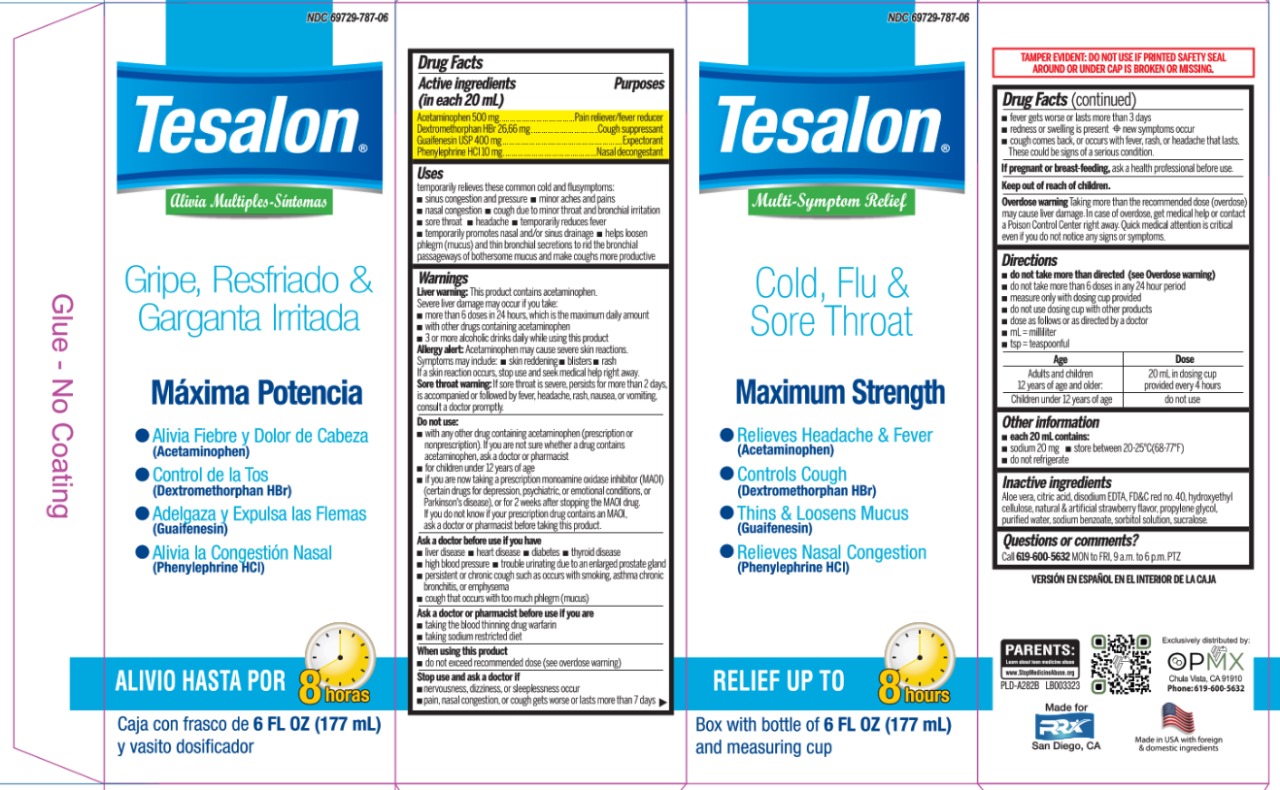 DRUG LABEL: Tesalon Jarabe Adulto
NDC: 69729-787 | Form: SYRUP
Manufacturer: OPMX LLC
Category: otc | Type: HUMAN OTC DRUG LABEL
Date: 20241007

ACTIVE INGREDIENTS: ACETAMINOPHEN 500 mg/20 mL; DEXTROMETHORPHAN HYDROBROMIDE 26.66 mg/20 mL; PHENYLEPHRINE HYDROCHLORIDE 10 mg/20 mL; GUAIFENESIN 400 mg/20 mL
INACTIVE INGREDIENTS: ALOE; ANHYDROUS CITRIC ACID; HYDROXYETHYL CELLULOSE, UNSPECIFIED; SORBITOL SOLUTION; EDETATE DISODIUM; FD&C RED NO. 4; PROPYLENE GLYCOL; WATER; SODIUM BENZOATE; SUCRALOSE

Tesalon Multi Symptom Relief

Active ingredients

Purposes

Active ingredients (in each 20mL) | Purposes
Acetaminophen 500 mg | Pain reliever/fever reducer
Dextromethorphan HBr 26.66 mg | Cough suppressant
Guaifenesin USP 400 mg | Expectorant
Phenylephrine Cl 10 mg | Nasal decongestant

Uses

temporarily relieves these common cold and flu symptoms:

sinus congestion and pressure
minor aches and pains
nasal congestion
cough due to minor throat and bronchial irritation
sore throat
headache
temporarily reduces fever
temporarily promotes nasal and/or sinus drainage
helps loosen phlegm (mucus) and thin bronchial secretions to rid the bronchial passageways of bothersome mucus and make coughs more productive

Warnings

Liver warning

This product contains acetaminophen.

Severe liver damage may occur if you take:

more than 6 doses in 24 hours, which is the maximum daily amount
with other drugs containing acetaminophen
3 or more alcoholic drinks daily while using this product

Allergy allert

Acetaminophen may cause severe skin reactions.

Symptoms may include:

skin reddening
blisters
rash
If a skin reaction occurs, stop use and seek medical help right away.

Sore throat warning

if sore throat is severe, persists for more than 2 days, is accompanied or followed by fever, headache, rash, nausea, or vomiting, consult a doctor promptly.

Do not use

with any other drug containing acetaminophen (prescription or nonprescription). If you are not sure whether a drug contains acetaminophen, ask a doctor or pharmacist
for children under 12 years of age
if you are now taking a prescription monoamine oxidase inhibitor (MAOI) (certain drugs for depression, psychiatric, or emotional conditions, or Parkison´s disease), or for 2 weeks after stopping the MAOI drug. If you do not know if your prescription drug contains an MAOI, ask a doctor or pharmacist before taking this product.

Ask a doctor before use if you have

liver disease
heart disease
diabetes
thyroid disease
high blood pressure
trouble urinating due to an enlarged prostate gland
persistent or chronic cough such as occurs with smoking, asthma chronic bronchitis, or emphysema
cough that occurs with too much phlegm (mucus)

Ask a doctor or pharmacist before use if you are

taking the blood thinning drug warfarin, taking sodium restricted diet.

Stop use and ask a doctor if

nervousness, dizziness, or sleeplessness occur
pain, nasal congestion, or cough gets worse or lasts more than 7 days
fever gets worse or lasts more than 3 days
redness or swelling is present
new symptoms occur
cough comes back, or occurs with fever, rash, or headache that lasts.
These could be signs of a serious condition.

If pregnant or breast-feeding,

ask health professional before use

Keep out of reach of children

Overdose warning

Taking more than the recommended dose (overdose) may cause liver damage. In case of overdose, get medical help or contact a Poison Control Center right away. Quick medical attention is critical even if you do not notice any signs or symptoms.

Directions

do not take more than directed (see Overdose warning)
do not take more than 6 doses in any 24 hour period
measure only with dosing cup provided
do not use dosing cup with other products
dose as follows or as directed by a doctor
mL=milliliter
tsp=teaspoonful

Age.............................. Dose

Adults and children 12 years of age and older 20 mL in dosing cup provided every 4 hours

Children under 12 years of age do not use

Other information

each 10 mL contains:
sodium 10mg
store between 20-25°C (68-77°F)
do not refrigerate
keep carton for complete Drug Facts

Inactive ingredients

Aloe vera, citric acid, disodium EDTA, FD&C red no 40, hydroxyethyl cellulose, natural & artificial strawberry flavor, propylene glycol, purified water, sodium benzoate, sorbitol solution, sucralose.

Questions or comments?

Call 619-600-5632 MON to FRI, 9 a.m. to 6 p.m. PTZ

PACKAGE LABEL

NDC 69729-787-06

Tesalon®

Alivia Múltiples-Síntomas

Gripe, Resfriado & Garganta Irritada

Máxima Potencia

Alivia Fiebre y Dolor de Cabeza
(Acetaminophen)

Control de la Tos
(Dextromethorphan HBr)

Adelgaza y Expulsa las Flemas
(Guaifenesin)

Alivia la Congestión Nasal
(Phenylephrine HCl)

Alivio hasta por 8 horas

Caja con frasco de 6FL OZ (177mL)

y vasito dosificador

NDC 69729-787-06

Tesalon®

Multi-Sympton Relief

Cold, Flu & Sore Throat

Maximum Strength

Relieves Headache & Fever
(Acetaminophen)

Controls Cough
(Dextromethorphan HBr)

Thins & Loosens Mucus
(Guaifenesin)

Relieves Nasal Congestion
(Phenylephrine HCl)

Relief up to 8 hours

Box with bottle of 6 FL OZ (177mL)

and measuring cup

Tampering evident: DO NOT USE IF PRINTED SAFETY SEAL AROUND OR UNDER CAP IS BROKEN OR MISSING.

VERSIÓN EN ESPAÑOL EN EL INTERIOR DE LA CAJA